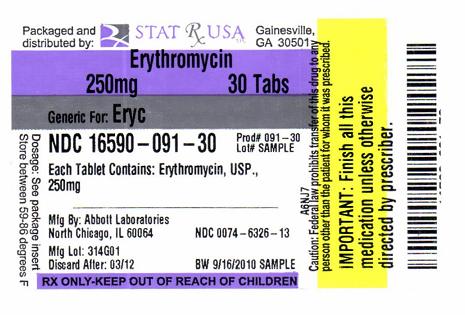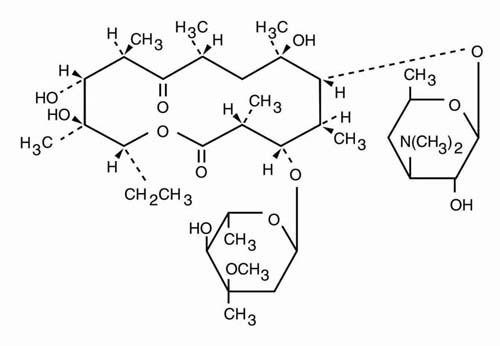 DRUG LABEL: ERYTHROMYCIN
NDC: 16590-091 | Form: TABLET, FILM COATED
Manufacturer: STAT RX USA LLC
Category: prescription | Type: HUMAN PRESCRIPTION DRUG LABEL
Date: 20110303

ACTIVE INGREDIENTS: ERYTHROMYCIN 250 mg/1 1
INACTIVE INGREDIENTS: COLLOIDAL SILICON DIOXIDE; CROSCARMELLOSE SODIUM; CROSPOVIDONE; HYDROXYPROPYL CELLULOSE; HYPROMELLOSES; MAGNESIUM STEARATE; CELLULOSE, MICROCRYSTALLINE; POVIDONE; POLYETHYLENE GLYCOL; PROPYLENE GLYCOL; SODIUM CITRATE; SODIUM HYDROXIDE; SORBIC ACID; SORBITAN MONOOLEATE; TITANIUM DIOXIDE

To reduce the development of drug-resistant bacteria and maintain the effectiveness of Erythromycin Base Filmtab tablets and other antibacterial drugs, Erythromycin Base Filmtab tablets would be used only to treat or prevent infections that are proven or strongly suspected to be caused by bacteria.

DESCRIPTION

Erythromycin Base Filmtab (erythromycin tablets, USP) is an antibacterial product containing erythromycin, USP, in a unique, nonenteric film coating for oral administration. Erythromycin Base Filmtab tablets are available in two strengths containing either 250 mg or 500 mg of erythromycin base.

Erythromycin is produced by a strain of Saccharopolyspora erythraea (formerly Streptomyces erythraeus) and belongs to the macrolide group of antibiotics. It is basic and readily forms salts with acids. Erythromycin is a white to off-white powder, slightly soluble in water, and soluble in alcohol, chloroform, and ether. Erythromycin is known chemically as (3R*, 4S*, 5S*, 6R*, 7R*, 9R*, 11R*, 12R*, 13S*, 14R*)-4-[(2,6-dideoxy-3-C-methyl-3-O-methyl-α-L-ribo-hexopyranosyl)oxy]-14-ethyl-7,12,13-trihydroxy-3,5,7,9,11,13-hexamethyl-6-[[3,4,6-trideoxy-3-(dimethylamino)-β-D-xylo-hexopyranosyl]oxy]oxacyclotetradecane-2,10-dione. The molecular formula is C37H67NO13, and the molecular weight is 733.94. The structural formula is:

Inactive Ingredients

Colloidal silicon dioxide, croscarmellose sodium, crospovidone, D and C Red No. 30 Aluminum Lake, hydroxypropyl cellulose, hypromellose, hydroxypropyl methylcellulose phthalate, magnesium stearate, microcrystalline cellulose, povidone, polyethylene glycol, propylene glycol, sodium citrate, sodium hydroxide, sorbic acid, sorbitan monooleate, talc, and titanium dioxide.

CLINICAL PHARMACOLOGY

Orally administered erythromycin base and its salts are readily absorbed in the microbiologically active form. Interindividual variations in the absorption of erythromycin are, however, observed, and some patients do not achieve optimal serum levels. Erythromycin is largely bound to plasma proteins. After absorption, erythromycin diffuses readily into most body fluids. In the absence of meningeal inflammation, low concentrations are normally achieved in the spinal fluid but the passage of the drug across the blood-brain barrier increases in meningitis. Erythromycin crosses the placental barrier, but fetal plasma levels are low. The drug is excreted in human milk. Erythromycin is not removed by peritoneal dialysis or hemodialysis.

In the presence of normal hepatic function, erythromycin is concentrated in the liver and is excreted in the bile; the effect of hepatic dysfunction on biliary excretion of erythromycin is not known. After oral administration, less than 5% of the administered dose can be recovered in the active form in the urine.

Optimal blood levels are obtained when Erythromycin Base Filmtab tablets are given in the fasting state (at least ½ hour and preferably 2 hours before meals). Bioavailability data are available from Abbott Laboratories, Dept. 42W.

Microbiology

Erythromycin acts by inhibition of protein synthesis by binding 50 S ribosomal subunits of susceptible organisms. It does not affect nucleic acid synthesis. Antagonism has been demonstrated in vitro between erythromycin and clindamycin, lincomycin, and chloramphenicol.

Many strains of Haemophilus influenzae are resistant to erythromycin alone but are susceptible to erythromycin and sulfonamides used concomitantly.

Staphylococci resistant to erythromycin may emerge during a course of erythromycin therapy.

Erythromycin has been shown to be active against most strains of the following microorganisms, both in vitro and in clinical infections as described in the INDICATIONS AND USAGE section.

Gram-positive organisms

Corynebacterium diphtheriae

Corynebacterium minutissimum

Listeria monocytogenes

Staphylococcus aureus (resistant organisms may emerge during treatment)

Streptococcus pneumoniae

Streptococcus pyogenes

Gram-negative organisms

Bordetella pertussis

Legionella pneumophila

Neisseria gonorrhoeae

Other microorganisms

Chlamydia trachomatis

Entamoeba histolytica

Mycoplasma pneumoniae

Treponema pallidum

Ureaplasma urealyticum

The following in vitro data are available, but their clinical significance is unknown.

Erythromycin exhibits in vitro minimal inhibitory concentrations (MIC's) of 0.5 µg/mL or less against most (≥ 90%) strains of the following microorganisms; however, the safety and effectiveness of erythromycin in treating clinical infections due to these microorganisms have not been established in adequate and well-controlled clinical trials.

Gram-positive organisms

Viridans group streptococci

Gram-negative organisms

Moraxella catarrhalis

Susceptibility Tests
Dilution Techniques

Quantitative methods are used to determine antimicrobial minimum inhibitory concentrations (MIC's). These MIC's provide estimates of the susceptibility of bacteria to antimicrobial compounds. The MIC's should be determined using a standardized procedure. Standardized procedures are based on a dilution method^1 (broth or agar) or equivalent with standardized inoculum concentrations and standardized concentrations of erythromycin powder. The MIC values should be interpreted according to the following criteria:

MIC (µg/mL) | Interpretation
≤ 0.5 | Susceptible (S)
1-4 | Intermediate (I)
≥ 8 | Resistant (R)

A report of "Susceptible" indicates that the pathogen is likely to be inhibited if the antimicrobial compound in the blood reaches the concentrations usually achievable. A report of "Intermediate" indicates that the result should be considered equivocal, and, if the microorganism is not fully susceptible to alternative, clinically feasible drugs, the test should be repeated. This category implies possible clinical applicability in body sites where the drug is physiologically concentrated or in situations where high dosage of drug can be used. This category also provides a buffer zone which prevents small uncontrolled technical factors from causing major discrepancies in interpretation. A report of "Resistant" indicates that the pathogen is not likely to be inhibited if the antimicrobial compound in the blood reaches the concentrations usually achievable; other therapy should be selected.

Standardized susceptibility test procedures require the use of laboratory control microorganisms to control the technical aspects of the laboratory procedures. Standard erythromycin powder should provide the following MIC values:

Microorganism | MIC (µg/mL)
S. aureus ATCC 29213 | 0.12-0.5
E. faecalis ATCC 29212 | 1-4

Diffusion Techniques

Quantitative methods that require measurement of zone diameters also provide reproducible estimates of the susceptibility of bacteria to antimicrobial compounds. One such standardized procedure^2 requires the use of standardized inoculum concentrations. This procedure uses paper disks impregnated with 15-µg erythromycin to test the susceptibility of microorganisms to erythromycin.

Reports from the laboratory providing results of the standard single-disk susceptibility test with a 15-µg erythromycin disk should be interpreted according to the following criteria:

Zone Diameter (mm) | Interpretation
≥ 23 | Susceptible (S)
14-22 | Intermediate (I)
≤ 13 | Resistant (R)

Interpretation should be as stated above for results using dilution techniques. Interpretation involves correlation of the diameter obtained in the disk test with the MIC for erythromycin.

As with standardized dilution techniques, diffusion methods require the use of laboratory control microorganisms that are used to control the technical aspects of the laboratory procedures. For the diffusion technique, the 15-µg erythromycin disk should provide the following zone diameters in these laboratory test quality control strains:

Microorganism | Zone Diameter (mm)
S. aureus ATCC 25923 | 22-30

INDICATIONS AND USAGE

To reduce the development of drug-resistant bacteria and maintain the effectiveness of Erythromycin Base Filmtab tablets and other antibacterial drugs, Erythromycin Base Filmtab tablets should be used only to treat or prevent infections that are proven or strongly suspected to be caused by susceptible bacteria. When culture and susceptibility information are available, they should be considered in selecting or modifying antibacterial therapy. In the absence of such data, local epidemiology and susceptibility patterns may contribute to the empiric selection of therapy.

Erythromycin Base Filmtab tablets are indicated in the treatment of infections caused by susceptible strains of the designated microorganisms in the diseases listed below:

Upper respiratory tract infections of mild to moderate degree caused by Streptococcus pyogenes; Streptococcus pneumoniae; Haemophilus influenzae (when used concomitantly with adequate doses of sulfonamides, since many strains of H. influenzae are not susceptible to the erythromycin concentrations ordinarily achieved). (See appropriate sulfonamide labeling for prescribing information.)

Lower respiratory tract infections of mild to moderate severity caused by Streptococcus pyogenes or Streptococcus pneumoniae.

Listeriosis caused by Listeria monocytogenes.

Respiratory tract infections due to Mycoplasma pneumoniae.

Skin and skin structure infections of mild to moderate severity caused by Streptococcus pyogenes or Staphylococcus aureus (resistant staphylococci may emerge during treatment).

Pertussis (whooping cough) caused by Bordetella pertussis. Erythromycin is effective in eliminating the organism from the nasopharynx of infected individuals, rendering them noninfectious. Some clinical studies suggest that erythromycin may be helpful in the prophylaxis of pertussis in exposed susceptible individuals.

Diphtheria: Infections due to Corynebacterium diphtheriae , as an adjunct to antitoxin, to prevent establishment of carriers and to eradicate the organism in carriers.

Erythrasma - In the treatment of infections due to Corynebacterium minutissimum.

Intestinal amebiasis caused by Entamoeba histolytica (oral erythromycins only). Extraenteric amebiasis requires treatment with other agents.

Acute pelvic inflammatory disease caused by Neisseria gonorrhoeae: Erythrocin® Lactobionate-I.V. (erythromycin lactobionate for injection, USP) followed by erythromycin base orally, as an alternative drug in treatment of acute pelvic inflammatory disease caused by N. gonorrhoeae in female patients with a history of sensitivity to penicillin. Patients should have a serologic test for syphilis before receiving erythromycin as treatment of gonorrhea and a follow-up serologic test for syphilis after 3 months.

Erythromycins are indicated for treatment of the following infections caused by Chlamydia trachomatis: conjunctivitis of the newborn, pneumonia of infancy, and urogenital infections during pregnancy. When tetracyclines are contraindicated or not tolerated, erythromycin is indicated for the treatment of uncomplicated urethral, endocervical, or rectal infections in adults due to Chlamydia trachomatis.^3

When tetracyclines are contraindicated or not tolerated, erythromycin is indicated for the treatment of nongonococcal urethritis caused by Ureaplasma urealyticum.^3

Primary syphilis caused by Treponema pallidum. Erythromycin (oral forms only) is an alternative choice of treatment for primary syphilis in patients allergic to the penicillins. In treatment of primary syphilis, spinal fluid should be examined before treatment and as part of the follow-up after therapy.

Legionnaires' Disease caused by Legionella pneumophila. Although no controlled clinical efficacy studies have been conducted, in vitro and limited preliminary clinical data suggest that erythromycin may be effective in treating Legionnaires' Disease.

Prophylaxis
Prevention of Initial Attacks of Rheumatic Fever

Penicillin is considered by the American Heart Association to be the drug of choice in the prevention of initial attacks of rheumatic fever (treatment of Streptococcus pyogenes infections of the upper respiratory tract e.g., tonsillitis, or pharyngitis).^3 Erythromycin is indicated for the treatment of penicillin-allergic patients. The therapeutic dose should be administered for ten days.

Prevention of Recurrent Attacks of Rheumatic Fever

Penicillin or sulfonamides are considered by the American Heart Association to be the drugs of choice in the prevention of recurrent attacks of rheumatic fever. In patients who are allergic to penicillin and sulfonamides, oral erythromycin is recommended by the American Heart Association in the long-term prophylaxis of streptococcal pharyngitis (for the prevention of recurrent attacks of rheumatic fever).^3

CONTRAINDICATIONS

Erythromycin is contraindicated in patients with known hypersensitivity to this antibiotic.

Erythromycin is contraindicated in patients taking terfenadine, astemizole, pimozide, or cisapride. (See PRECAUTIONS - Drug Interactions .)

WARNINGS

There have been reports of hepatic dysfunction, including increased liver enzymes, and hepatocellular and/or cholestatic hepatitis, with or without jaundice, occurring in patients receiving oral erythromycin products.

There have been reports suggesting that erythromycin does not reach the fetus in adequate concentration to prevent congenital syphilis. Infants born to women treated during pregnancy with oral erythromycin for early syphilis should be treated with an appropriate penicillin regimen.

Rhabdomyolysis with or without renal impairment has been reported in seriously ill patients receiving erythromycin concomitantly with lovastatin. Therefore, patients receiving concomitant lovastatin and erythromycin should be carefully monitored for creatine kinase (CK) and serum transaminase levels. (See package insert for lovastatin.)

Pseudomembranous colitis has been reported with nearly all antibacterial agents, including erythromycin, and may range in severity from mild to life threatening. Therefore, it is important to consider this diagnosis in patients who present with diarrhea subsequent to the administration of antibacterial agents.

Treatment with antibacterial agents alters the normal flora of the colon and may permit overgrowth of clostridia. Studies indicate that a toxin produced by Clostridium difficile is a primary cause of "antibiotic-associated colitis".

After the diagnosis of pseudomembranous colitis has been established, therapeutic measures should be initiated. Mild cases of pseudomembranous colitis usually respond to discontinuation of the drug alone. In moderate to severe cases, consideration should be given to management with fluids and electrolytes, protein supplementation, and treatment with an antibacterial drug clinically effective against Clostridium difficile colitis.

PRECAUTIONS

General

Prescribing Erythromycin Base Filmtab tablets in the absence of a proven or strongly suspected bacterial infection or a prophylactic indication is unlikely to provide benefit to the patient and increases the risk of the development of drug-resistant bacteria.

Since erythromycin is principally excreted by the liver, caution should be exercised when erythromycin is administered to patients with impaired hepatic function. (See CLINICAL PHARMACOLOGY and WARNINGS.)

There have been reports that erythromycin may aggravate the weakness of patients with myasthenia gravis.

There have been reports of infantile hypertrophic pyloric stenosis (IHPS) occurring in infants following erythromycin therapy. In one cohort of 157 newborns who were given erythromycin for pertussis prophylaxis, seven neonates (5%) developed symptoms of non-bilious vomiting or irritability with feeding and were subsequently diagnosed as having IHPS requiring surgical pyloromyotomy. A possible dose-response effect was described with an absolute risk of IHPS of 5.1% for infants who took erythromycin for 8-14 days and 10% for infants who took erythromycin for 15-21 days.^4 Since erythromycin may be used in the treatment of conditions in infants which are associated with significant mortality or morbidity (such as pertussis or neonatal Chlamydia trachomatis infections), the benefit of erythromycin therapy needs to be weighed against the potential risk of developing IHPS. Parents should be informed to contact their physician if vomiting or irritability with feeding occurs.

Prolonged or repeated use of erythromycin may result in an overgrowth of nonsusceptible bacteria or fungi. If superinfection occurs, erythromycin should be discontinued and appropriate therapy instituted.

When indicated, incision and drainage or other surgical procedures should be performed in conjunction with antibiotic therapy.

Information for Patients

Patients should be counseled that antibacterial drugs including Erythromycin Base Filmtab tablets should only be used to treat bacterial infections. They do not treat viral infections (e.g., the common cold). When Erythromycin Base Filmtab tablets is prescribed to treat a bacterial infection, patients should be told that although it is common to feel better early in the course of therapy, the medication should be taken exactly as directed. Skipping doses or not completing the full course of therapy may (1) decrease the effectiveness of the immediate treatment and (2) increase the likelihood that bacteria will develop resistance and will not be treatable by Erythromycin Base Filmtab tablets or other antibacterial drugs in the future.

Drug Interactions

Erythromycin use in patients who are receiving high doses of theophylline may be associated with an increase in serum theophylline levels and potential theophylline toxicity. In case of theophylline toxicity and/or elevated serum theophylline levels, the dose of theophylline should be reduced while the patient is receiving concomitant erythromycin therapy.

Concomitant administration of erythromycin and digoxin has been reported to result in elevated digoxin serum levels.

There have been reports of increased anticoagulant effects when erythromycin and oral anticoagulants were used concomitantly. Increased anticoagulation effects due to interactions of erythromycin with oral anticoagulants may be more pronounced in the elderly.

Erythromycin is a substrate and inhibitor of the 3A isoform subfamily of the cytochrome p450 enzyme system (CYP3A). Coadministration of erythromycin and a drug primarily metabolized by CYP3A may be associated with elevations in drug concentrations that could increase or prolong both the therapeutic and adverse effects of the concomitant drug. Dosage adjustments may be considered, and when possible, serum concentrations of drugs primarily metabolized by CYP3A should be monitored closely in patients concurrently receiving erythromycin.

The following are examples of some clinically significant CYP3A based drug interactions. Interactions with other drugs metabolized by the CYP3A isoform are also possible. The following CYP3A based drug interactions have been observed with erythromycin products in post-marketing experience:

Ergotamine/dihydroergotamine

Concurrent use of erythromycin and ergotamine or dihydroergotamine has been associated in some patients with acute ergot toxicity characterized by severe peripheral vasospasm and dysesthesia.

Triazolobenzodiazepines (Such as Triazolam and Alprazolam) and Related Benzodiazepines

Erythromycin has been reported to decrease the clearance of triazolam and midazolam, and thus, may increase the pharmacologic effect of these benzodiazepines.

HMG-CoA Reductase Inhibitors

Erythromycin has been reported to increase concentrations of HMG-CoA reductase inhibitors (e.g., lovastatin and simvastatin). Rare reports of rhabdomyolysis have been reported in patients taking these drugs concomitantly.

Sildenafil (Viagra)

Erythromycin has been reported to increase the systemic exposure (AUC) of sildenafil. Reduction of sildenafil dosage should be considered. (See Viagra package insert.)

There have been spontaneous or published reports of CYP3A based interactions of erythromycin with cyclosporine, carbamazepine, tacrolimus, alfentanil, disopyramide, rifabutin, quinidine, methylprednisolone, cilostazol, vinblastine, and bromocriptine.

Concomitant administration of erythromycin with cisapride, pimozide, astemizole, or terfenadine is contraindicated. (See CONTRAINDICATIONS.)

In addition, there have been reports of interactions of erythromycin with drugs not thought to be metabolized by CYP3A, including hexobarbital, phenytoin, and valproate.

Erythromycin has been reported to significantly alter the metabolism of the nonsedating antihistamines terfenadine and astemizole when taken concomitantly. Rare cases of serious cardiovascular adverse events, including electrocardiographic QT/QTc interval prolongation, cardiac arrest, torsades de pointes, and other ventricular arrhythmias, have been observed. (See CONTRAINDICATIONS.) In addition, deaths have been reported rarely with concomitant administration of terfenadine and erythromycin.

There have been post-marketing reports of drug interactions when erythromycin was co-administered with cisapride, resulting in QT prolongation, cardiac arrhythmias, ventricular tachycardia, ventricular fibrillation, and torsades de pointes, most likely due to the inhibition of hepatic metabolism of cisapride by erythromycin. Fatalities have been reported. (See CONTRAINDICATIONS).

Drug/Laboratory Test Interactions

Erythromycin interferes with the fluorometric determination of urinary catecholamines.

Carcinogenesis, Mutagenesis, Impairment of Fertility

Long-term (2-year) oral studies conducted in rats with erythromycin base did not provide evidence of tumorigenicity. Mutagenicity studies have not been conducted. There was no apparent effect on male or female fertility in rats fed erythromycin (base) at levels up to 0.25 percent of diet.

Pregnancy
Teratogenic effects
Pregnancy Category B

There is no evidence of teratogenicity or any other adverse effect on reproduction in female rats fed erythromycin base (up to 0.25 percent of diet) prior to and during mating, during gestation, and through weaning of two successive litters. There are, however, no adequate and well-controlled studies in pregnant women. Because animal reproduction studies are not always predictive of human response, this drug should be used during pregnancy only if clearly needed.

Labor and Delivery

The effect of erythromycin on labor and delivery is unknown.

Nursing Mothers

Erythromycin is excreted in human milk. Caution should be exercised when erythromycin is administered to a nursing woman.

Pediatric Use

See INDICATIONS AND USAGEand DOSAGE AND ADMINISTRATION.

ADVERSE REACTIONS

The most frequent side effects of oral erythromycin preparations are gastrointestinal and are dose-related. They include nausea, vomiting, abdominal pain, diarrhea and anorexia. Symptoms of hepatitis, hepatic dysfunction and/or abnormal liver function test results may occur. (See WARNINGS.)

Onset of pseudomembranous colitis symptoms may occur during or after antibacterial treatment. (See WARNINGS.)

Erythromycin has been associated with QT prolongation and ventricular arrhythmias, including ventricular tachycardia and torsades de pointes.

Allergic reactions ranging from urticaria to anaphylaxis have occurred. Skin reactions ranging from mild eruptions to erythema multiforme, Stevens-Johnson syndrome, and toxic epidermal necrolysis have been reported rarely.

There have been rare reports of pancreatitis and convulsions.

There have been isolated reports of reversible hearing loss occurring chiefly in patients with renal insufficiency and in patients receiving high doses of erythromycin.

OVERDOSAGE

In case of overdosage, erythromycin should be discontinued. Overdosage should be handled with the prompt elimination of unabsorbed drug and all other appropriate measures should be instituted.

Erythromycin is not removed by peritoneal dialysis or hemodialysis.

DOSAGE AND ADMINISTRATION

Optimal blood levels are obtained when Erythromycin Base Filmtab tablets are given in the fasting state (at least ½ hour and preferably 2 hours before meals).

Adults

The usual dosage of Erythromycin Base Filmtab is one 250 mg tablet four times daily in equally spaced doses or one 500 mg tablet every 12 hours. Dosage may be increased up to 4 g per day according to the severity of the infection. However, twice-a-day dosing is not recommended when doses larger than 1 g daily are administered.

Children

Age, weight, and severity of the infection are important factors in determining the proper dosage. The usual dosage is 30 to 50 mg/kg/day, in equally divided doses. For more severe infections this dosage may be doubled but should not exceed 4 g per day.

In the treatment of streptococcal infections of the upper respiratory tract (e.g., tonsillitis or pharyngitis), the therapeutic dosage of erythromycin should be administered for at least ten days.

The American Heart Association suggests a dosage of 250 mg of erythromycin orally, twice a day in long-term prophylaxis of streptococcal upper respiratory tract infections for the prevention of recurring attacks of rheumatic fever in patients allergic to penicillin and sulfonamides.^3

Conjunctivitis of the Newborn Caused by Chlamydia trachomatis

Oral erythromycin suspension 50 mg/kg/day in 4 divided doses for at least 2 weeks.^3

Pneumonia of Infancy Caused by Chlamydia trachomatis

Although the optimal duration of therapy has not been established, the recommended therapy is oral erythromycin suspension 50 mg/kg/day in 4 divided doses for at least 3 weeks.

Urogenital Infections During Pregnancy Due to Chlamydia trachomatis

Although the optimal dose and duration of therapy have not been established, the suggested treatment is 500 mg of erythromycin by mouth four times a day on an empty stomach for at least 7 days. For women who cannot tolerate this regimen, a decreased dose of one erythromycin 500 mg tablet orally every 12 hours or 250 mg by mouth four times a day should be used for at least 14 days.^5

For adults with uncomplicated urethral, endocervical, or rectal infections caused by Chlamydia trachomatis, when tetracycline is contraindicated or not tolerated

500 mg of erythromycin by mouth four times a day for at least 7 days.^5

For patients with nongonococcal urethritis caused by Ureaplasma urealyticum when tetracycline is contraindicated or not tolerated

500 mg of erythromycin by mouth four times a day for at least seven days.^5

Primary Syphilis

30 to 40 g given in divided doses over a period of 10 to 15 days.

Acute Pelvic Inflammatory Disease Caused by N. gonorrhoeae

500 mg Erythrocin® Lactobionate-I.V. (erythromycin lactobionate for injection, USP) every 6 hours for 3 days, followed by 500 mg of erythromycin base orally every 12 hours for 7 days.

Intestinal Amebiasis Adults

500 mg every 12 hours or 250 mg every 6 hours for 10 to 14 days.

Children

30 to 50 mg/kg/day in divided doses for 10 to 14 days.

Pertussis

Although optimal dosage and duration have not been established, doses of erythromycin utilized in reported clinical studies were 40 to 50 mg/kg/day, given in divided doses for 5 to 14 days.

Legionnaires' Disease

Although optimal dosage has not been established, doses utilized in reported clinical data were 1 to 4 g daily in divided doses.

HOW SUPPLIED

Erythromycin Base Filmtab tablets (erythromycin tablets, USP) are supplied as pink, unscored oval tablets in the following strengths and packages.

250 mg tablets (debossed with Abbott “A” logo and EB):

Bottles of 100…...…………………………………………………..(NDC 0074-6326-13);

Bottles of 500……………………………………………………….(NDC 0074-6326-53);

ABBO-PAC® unit dose strip packages of 100 tablets……………...(NDC 0074-6326-11).

500 mg tablets (debossed with Abbott “A” logo and EA):

Bottles of 100……………………………………………………….(NDC 0074-6227-13).

Recommended Storage

Store below 86°F (30°C). Keep tightly closed.

REFERENCES

1. National Committee for Clinical Laboratory Standards. Methods for Dilution Antimicrobial Susceptibility Tests for Bacteria that Grow Aerobically, Third Edition. Approved Standard NCCLS Document M7-A3, Vol. 13, No. 25 NCCLS, Villanova , PA, December 1993.
2. National Committee for Clinical Laboratory Standards, Performance Standards for Antimicrobial Disk Susceptibility Tests, Fifth Edition. Approved Standard NCCLS Document M2-A5, Vol. 13, No. 24 NCCLS, Villanova , PA, December 1993.
3. Committee on Rheumatic Fever, Endocarditis, and Kawasaki Disease of the Council on Cardiovascular Disease in the Young, the American Heart Association: Prevention of Rheumatic Fever. Circulation. 78(4):1082-1086, October 1988.
4. Honein, M.A., et. al.: Infantile hypertrophic pyloric stenosis after pertussis prophylaxis with erythromycin: a case review and cohort study. The Lancet 1999;354 (9196):2101-5.
5. Data on file, Abbott Laboratories.

FILMTAB—Film-sealed tablets, Abbott.

Abbott Laboratories

North Chicago, IL 60064, U.S.A.